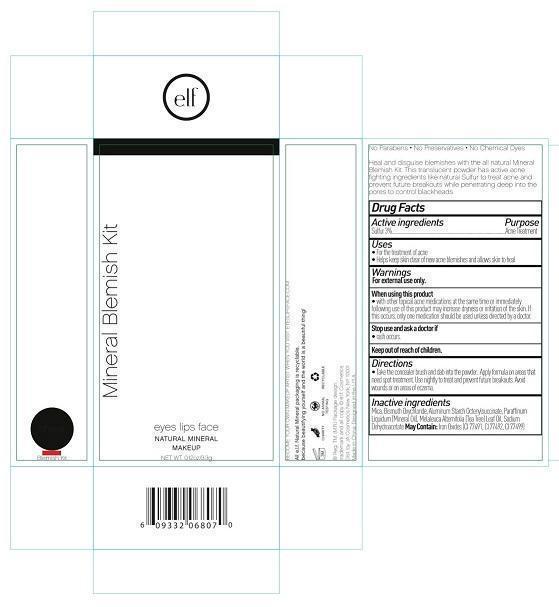 DRUG LABEL: MINERAL BLEMISH KIT
NDC: 76354-205 | Form: POWDER
Manufacturer: J. A. Cosmetics U.S. INC
Category: otc | Type: HUMAN OTC DRUG LABEL
Date: 20140319

ACTIVE INGREDIENTS: SULFUR 3 1/100 g
INACTIVE INGREDIENTS: MICA; BISMUTH OXYCHLORIDE; ALUMINUM STARCH OCTENYLSUCCINATE; MINERAL OIL; TEA TREE OIL; SODIUM DEHYDROACETATE; FERRIC OXIDE RED; FERRIC OXIDE YELLOW; FERROSOFERRIC OXIDE

Active Ingredient:

SULFUR (3%)

Purpose:

ACNE TREATMENT

Uses:

- FOR TREATMENT OF ACNE
- HELPS KEEP SKIN CLEAR OF NEW ACNE BLEMISHES AND ALLOWS SKIN TO HEAL

Warning:

For external use only

When Using This Product

- USING OTHER TROPICAL ACNE MEDICATIONS AT THE SAME TIME OR IMMEDIATELY FOLLOWING USE OF THIS PRODUCT MAY INCREASE DRYNESS OR IRRITATION OF SKIN. IF OCCURS, ONLY ONE MEDICATION SHOULD BE USED UNLESS DIRECTED BY A DOCTOR.

Stop use and ask a doctor if

- rash occurs.

KEEP OUT OF REACH OF CHILDREN.

Directions:

- TAKE THE CONCEALER BRUSH AND DAB INTO THE POWDER. APPLY FORMULA ON AREAS THAT NEED SPOT TREATMENT. USE NIGHTLY TO TREAT AND PREVENT FUTURE BREAKOUTS. AVOID WOUNDS OR ON AREAS OF ECZEMA.

Inactive Ingredient:

MICA, BISMUTH OXYCHLORIDE, ALUMINUM STARCH OCTENYLSUCCINATE, PARAFFINIUM LIQUIDUM (MINERAL OIL), MELALEUCA ALTERNIFOLIA (TEA TREE) LEAF OIL, SODIUM DEHYDROACETATE. MAY CONTAIN: IRON OXIDES (CI 77491, CI 77492, CI 77499)